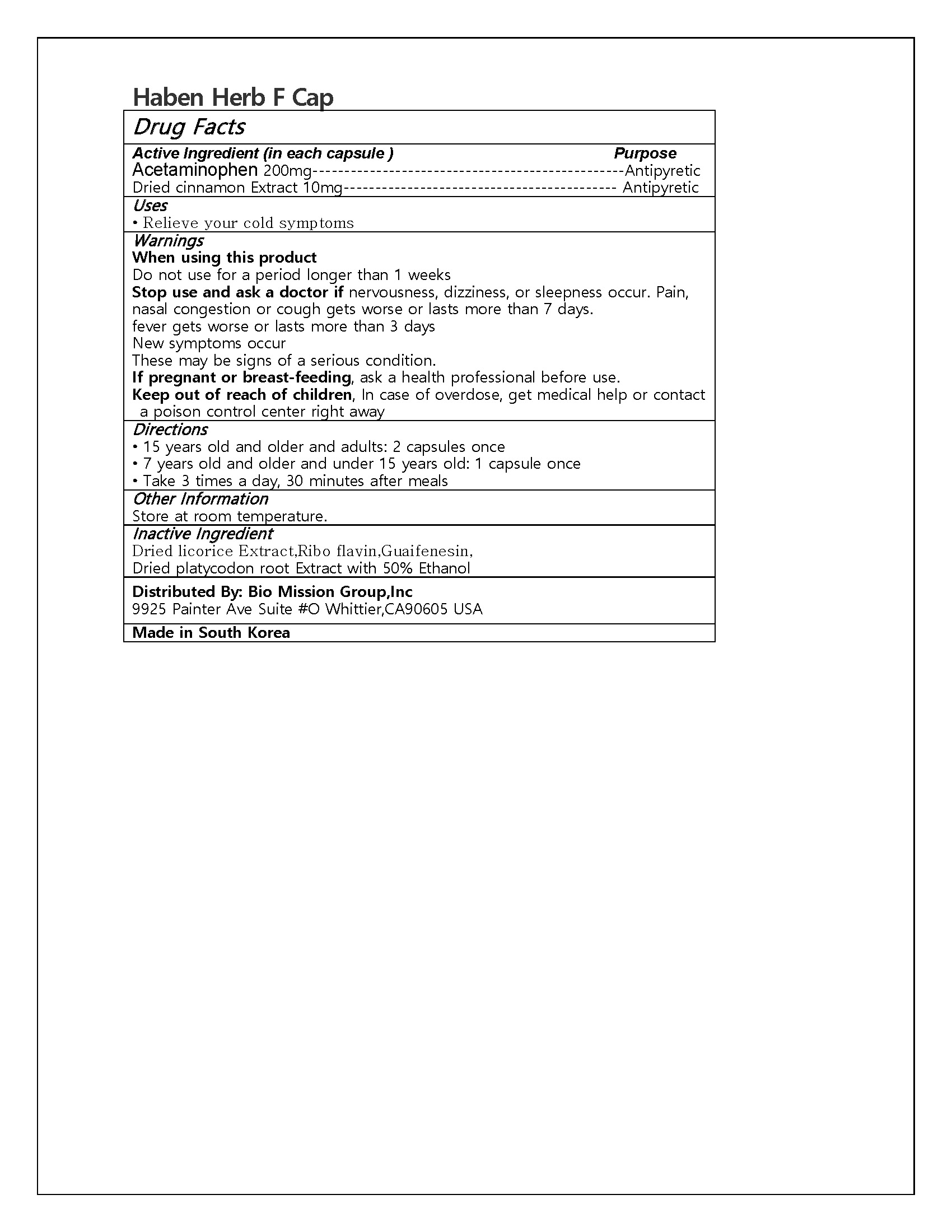 DRUG LABEL: Haben Herb F Cap
NDC: 72988-0040 | Form: CAPSULE
Manufacturer: Lydia Co., Ltd.
Category: otc | Type: HUMAN OTC DRUG LABEL
Date: 20240908

ACTIVE INGREDIENTS: CINNAMON 10 mg/1 1; ACETAMINOPHEN 200 mg/1 1
INACTIVE INGREDIENTS: GUAIFENESIN; SODIUM HYDROXIDE

ACTIVE INGREDIENT

Acetaminophen, Dried cinnamon Extract

PURPOSE

Relieve your cold symptoms

Keep out of reach of children

INDICATIONS AND USAGE

• 15 years old and older and adults: 2 capsules once

• 7 years old and older and under 15 years old: 1 capsule once

• Take 3 times a day, 30 minutes after meals

Warnings

For external use only.

Do not use in the eyes by putting this product into the rectum by using fingers or any mechanical device or applicator.

Ask a doctor before use if you have a vaginal discharge, rectal bleeding, diaper rash.

When using this product consult a doctor before exceeding recommended dosage.

Stop use and ask a doctor if condition gets worse, condition persists for more than 7 days, condition clears up and occurs again with within a few days. Do not begin to use any other hydrocortisone product unless you have consulted a doctor.

Keep out of reach of children. If swallowed, get medical help or contact a Poison Control Center right away.

INACTIVE INGREDIENT

Dried licorice Extract,Ribo flavin,Guaifenesin,

Dried platycodon root Extract with 50% Ethanol

DOSAGE AND ADMINISTRATION

for topical use